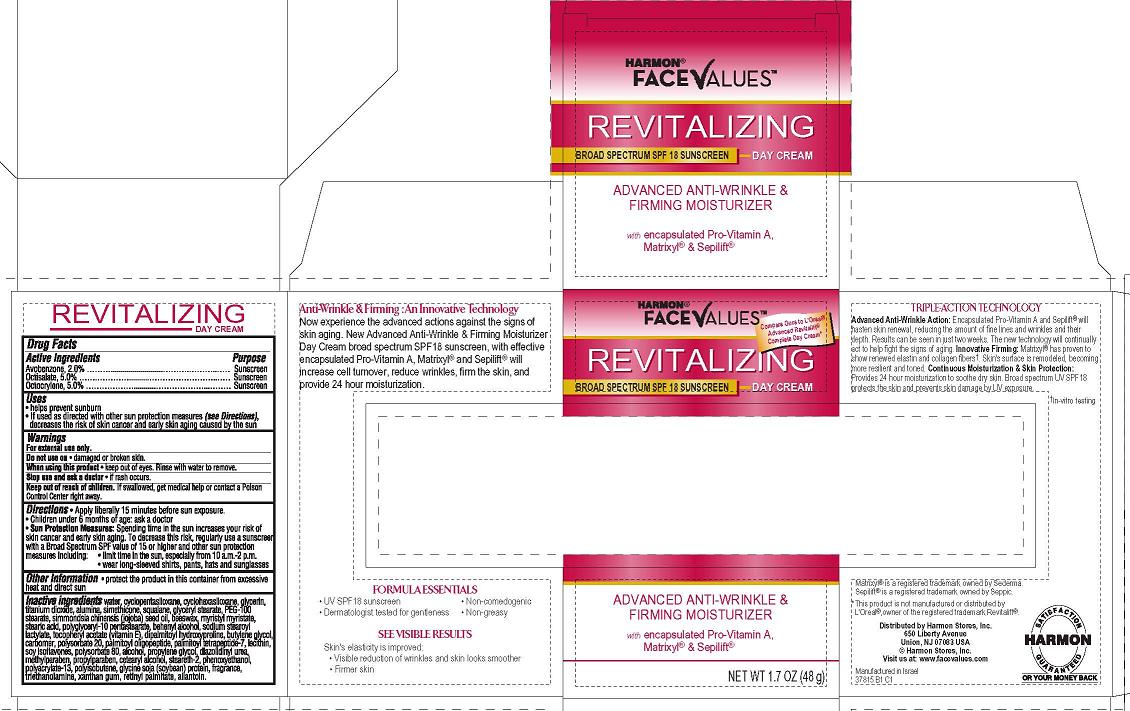 DRUG LABEL: Harmon Face Values Revitalizing Day
NDC: 63940-387 | Form: CREAM
Manufacturer: Harmon Stores Inc.
Category: otc | Type: HUMAN OTC DRUG LABEL
Date: 20120612

ACTIVE INGREDIENTS: AVOBENZONE 2 g/100 g; OCTISALATE 5 g/100 g; OCTOCRYLENE 5 g/100 g
INACTIVE INGREDIENTS: WATER; CYCLOMETHICONE 5; GLYCERIN; TITANIUM DIOXIDE; ALUMINUM OXIDE; GLYCERYL MONOSTEARATE; DIMETHICONE; PEG-100 STEARATE; CARBOMER COPOLYMER TYPE A (ALLYL PENTAERYTHRITOL CROSSLINKED); JOJOBA OIL; YELLOW WAX; MYRISTYL MYRISTATE; STEARIC ACID; BENZYL ALCOHOL; POLYSORBATE 20; SODIUM STEAROYL LACTYLATE; .ALPHA.-TOCOPHEROL ACETATE; DIPALMITOYL HYDROXYPROLINE; BUTYLENE GLYCOL; PALMITOYL OLIGOPEPTIDE; PALMITOYL TETRAPEPTIDE-7; LECITHIN, SOYBEAN; SOY ISOFLAVONES; POLYSORBATE 80; ALCOHOL; PROPYLENE GLYCOL; DIAZOLIDINYL UREA; METHYLPARABEN; PROPYLPARABEN; CETOSTEARYL ALCOHOL; STEARETH-2; PHENOXYETHANOL; POLYISOBUTYLENE (1000 MW); SOY PROTEIN; TROLAMINE; XANTHAN GUM; VITAMIN A PALMITATE; ALLANTOIN; SQUALANE; CYCLOMETHICONE 6

Harmon Face Values Revitalizing Day Cream Broad Spectrum SPF 18 Sunscreen

Active ingredient

Avobenzone 3.0%

Octisalate 5.0%

Octocrylene 10.0%

Purpose

Sunscreen

Uses

Helps prevent sunburn

If used as directed with other sun protection measures (see Directions), decreases the risk of skin cancer and early skin aging caused by the sun

Warnings

For external use only.

Do not use on damaged or broken skin.

When using this product keep out of eyes. Rinse with water to remove.

Stop use and ask a doctor if rash occurs.

Keep Out of Reach of Children. If swallowed, get medical help or contact a Poison Control Center right away.

Directions

Apply liberally 15 minutes before sun exposure.

Children under 6 months of age: ask a doctor.

Sun Protection Measures: Spending time in the sun increases your risk of skin cancer and early skin aging. To decrease this risk, regularly use a sunscreen with a Broad Spectrum SPF value of 15 or higher and other sun protection measures including:

- limit time in the sun, especially from 10 a.m. - 2 p.m.
- wear long-sleeved shirts, pants, hats and sunglasses

Inactive ingredients

water, disopropyl adipate, cyclopentasiloxane, glycerin, glyceryl stearate, PEG-100 stearate, titanium dioxide, alumina, simethicone, polymethyl methacrylate, phenoxyethanol, benzyl alcohol, triethanolamine, acrylates/C10-30 aklyl acrylate crosspolymer, tocopheryl acetate (vitamin E), carbomer, disodium EDTA

Package/Label Principal Display Panel

HARMON®
FACEVALUESTM

REVITALIZING

BROAD SPECTRUM SPF 18 SUNSCREEN DAY CREAM

ADVANCED ANTI-WRINKLE &
FIRMING MOISTURIZER

with encapsulated Pro-Vitamin A,
Matrixyl® & Sepilift®

Distributed by
Harmon Stores, Inc.
650 Liberty Ave.
Union, NJ 07083 USA
Harmon Stores, Inc.
Visit us at:
www.facevalues.com
Manufactured in Israel
37815B1C1

Carton Label